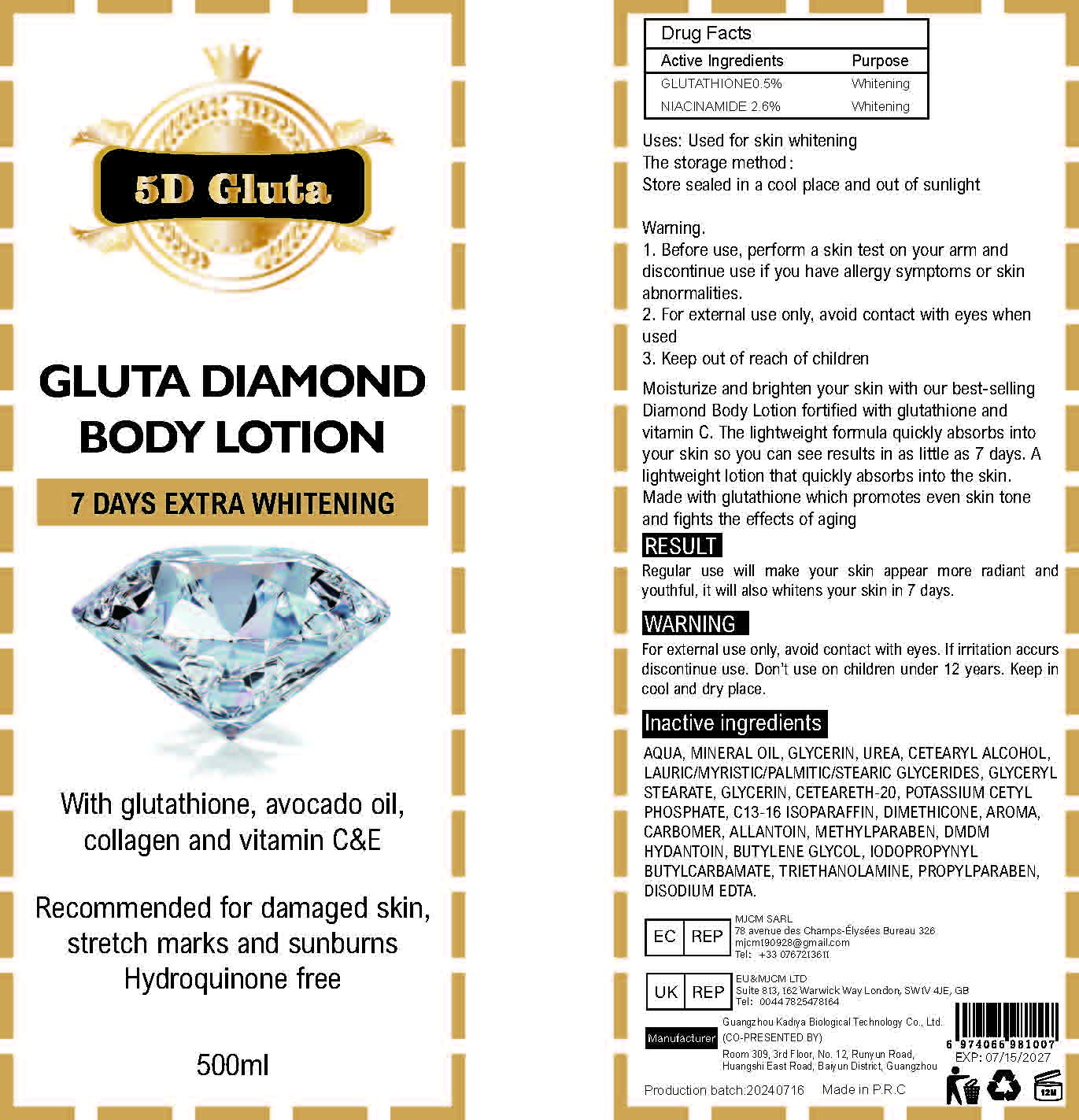 DRUG LABEL: 7 Days Extra Whitening BodyLotion
NDC: 84423-027 | Form: EMULSION
Manufacturer: Guangzhou Kadiya Biotechnology Co., Ltd.
Category: otc | Type: HUMAN OTC DRUG LABEL
Date: 20240723

ACTIVE INGREDIENTS: NIACINAMIDE 13 mg/500 mL; GLUTATHIONE 2.5 mg/500 mL
INACTIVE INGREDIENTS: IODOPROPYNYL BUTYLCARBAMATE; PROPYLPARABEN; GLYCERIN; DIMETHICONE; POLYOXYL 20 CETOSTEARYL ETHER; POTASSIUM CETYL PHOSPHATE; METHYLPARABEN; TROLAMINE; MINERAL OIL; CETOSTEARYL ALCOHOL; BUTYLENE GLYCOL; EDETATE DISODIUM; WATER; ALLANTOIN; UREA; GLYCERYL MONOSTEARATE; DMDM HYDANTOIN; C13-16 ISOPARAFFIN; CARBOXYPOLYMETHYLENE

Uses：
Used for skin whitening

INACTIVE INGREDIENT

AQUA、MINERAL OIL、GLYCERIN、UREA、CETEARYL ALCOHOL、LAURIC/MYRISTIC/PALMITIC/STEARIC GLYCERIDES、GLYCERYL STEARATE、GLYCERIN、CETEARETH-20、POTASSIUM CETYL PHOSPHATE、C13-16 ISOPARAFFIN、DIMETHICONE、AROMA、CARBOMER、ALLANTOIN、METHYLPARABEN、DMDM HYDANTOIN、BUTYLENE GLYCOL、IODOPROPYNYL BUTYLCARBAMATE、TRIETHANOLAMINE、PROPYLPARABEN、DISODIUM EDTA

Warning.
1.Before use, perform a skin test on your arm and discontinue use if you have allergy symptoms or skin abnormalities.
2、For external use only, avoid contact with eyes when used
3、Keep out of reach of children

INDICATIONS AND USAGE

On previously cleansed skin, apply your extreme shine bodymilk morning and evening, visible result after 7 days of use.

KEEP OUT OF REACH OF CHILDREN SECTION

Active Ingredients
GLUTATHIONE 0.5%
NIACINAMIDE 2.6%

DOSAGE AND ADMINISTRATION

On previously cleansed skin, apply your extreme shine bodymilk morning and evening, visible result after 7 days of use.

Drug Facts
Active Ingredients
GLUTATHIONE 0.5%
NIACINAMIDE 2.6%

Uses：
Used for skin whitening
The storage method：
Store sealed in a cool place and out of sunlight

Warning.
1.Before use, perform a skin test on your arm and discontinue use if you have allergy symptoms or skin abnormalities.
2、For external use only, avoid contact with eyes when used
3、Keep out of reach of children

Inactive ingredients：
AQUA、MINERAL OIL、GLYCERIN、UREA、CETEARYL ALCOHOL、LAURIC/MYRISTIC/PALMITIC/STEARIC GLYCERIDES、GLYCERYL STEARATE、GLYCERIN、CETEARETH-20、POTASSIUM CETYL PHOSPHATE、C13-16 ISOPARAFFIN、DIMETHICONE、AROMA、CARBOMER、ALLANTOIN、METHYLPARABEN、DMDM HYDANTOIN、BUTYLENE GLYCOL、IODOPROPYNYL BUTYLCARBAMATE、TRIETHANOLAMINE、PROPYLPARABEN、DISODIUM EDTA